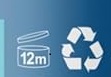 DRUG LABEL: Stay Minoxidil Hair Regrowth Treatment
NDC: 87210-351 | Form: LIQUID
Manufacturer: HALORIA INC.
Category: otc | Type: HUMAN OTC DRUG LABEL
Date: 20251021

ACTIVE INGREDIENTS: MINOXIDIL 5 mg/60 mL
INACTIVE INGREDIENTS: CETYL ALCOHOL; CITRIC ACID; LACTIC ACID; DEHYDRATED ALCOHOL; POLYSORBATE 60; RICINUS COMMUNIS (CASTOR) SEED OIL

ACTIVE INGREDIENT

BIOTIN 5%

PURPOSE

Anti-hair loss shampoo

INDICATIONS AND USAGE

1.Massage the scalp to fully relax the scalp
2.Ad one or two drops to the scalp area to be used.
3. Apply evenly to the rest of the area.
4.Continue to use weice a day

WARNINGS

For external use only.For external use only Keep away from fire and flame

KEEP OUT OF REACH OF CHILDREN

If swallowed, get medical help or contact a Poison Control Center right away.

WHEN USING

1. Do not apply on other parts of the body, For topical use only on the scalp
2. Avoid contact with the eyes in case of accidental contact rinse eyes with large arnounts of cool tap water.
3.Some people have experienced changes in hair color and'or texture.
4. The amount of hair rearowth is dlfferent for each person, This product will not work for all men.
Usage.1. Massage the scalp to fuly relaxthe scalp.2.Ad one ortwo dropsto the scap areato be used.3. Apply evenly to the rest ofthe area.4. Continue to use weice a day.
Fniendly reminder.it talkes time to regrow hail,it usually takes 45-60 days to see the effect, the speciflc effect will vary from person to person, some peole may need 90 days to see the effect

DO NOT USE

You have no family history of hair loss,hair loss is sudden and/or patchy
You do not know the reason for you hair loss.
You ae under 18 years of age, Do not use it on babies and children your scalp is red.inflamed.infected, irritated, or painful
You use other medicines on the scalp.Ask a doctor before use if you hace heart disease.

STOP USE

Chest pain, rapid heart beat, faintness, or dizziness occurs sudden, unexplained weight gain occurs,your hands or feet swell.

DOSAGE AND ADMINISTRATION

Twice each day,4 sprays (1ml)each time. 30 days supply

INACTIVE INGREDIENT

Cetyl Alcohol,Citric Acid ,Dehydrated Alcohol,Lactic Acid,Polysorbate 60,

Ricinus Communis (Castor) Seed Oil,Polygonum Multiflorum Root Extract,Zingiber Officinale (Ginger) Root Extract,Artemisia Vulgaris Extract,Ligusticum Chuanxiong Root Extract,Salvia Miltiorrhiza Root Extract,Angelica Polymorpha Sinensis Root Extract,Morus Nigra Fruit Extract,Panax Ginseng Root Extract,Houttuynia Cordata Extract,Carthamus Tinctorius (Safflower) Extract,Astragalus Membranaceus Root Extract,Camellia Japonica Seed Extract,Polygonatum Sibiricum Extract,Sophora Flavescens Root Extract,Panax Notoginseng Root Extract,Ganoderma Sinensis Extract,Portulaca Oleracea Extract,Cordyceps Sinensis Extract,Rehmannia Glutinosa Root Extract.